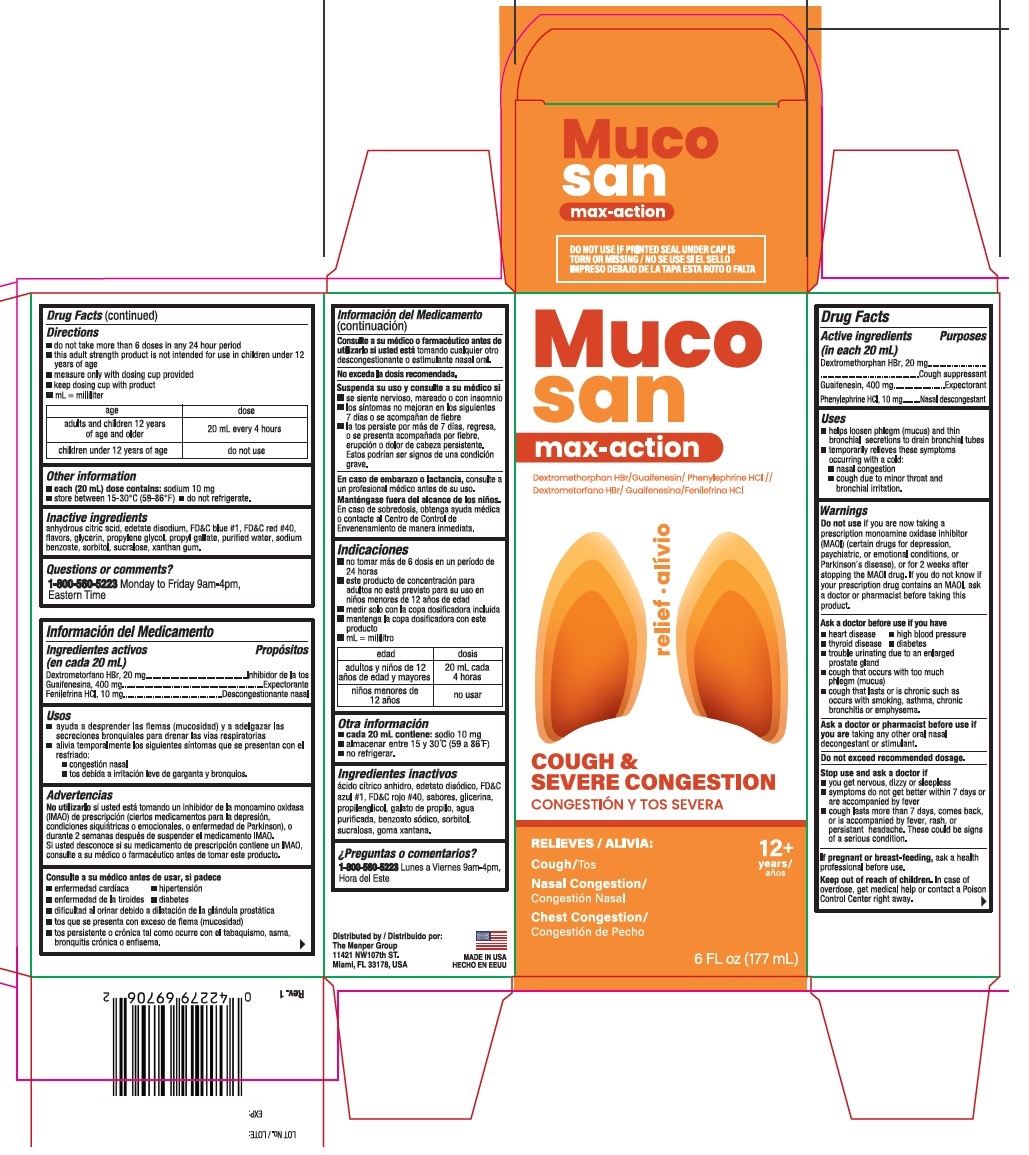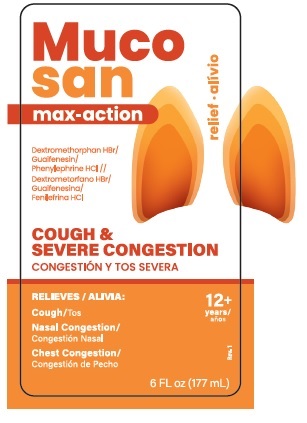 DRUG LABEL: Mucosan Severe Multi-Symptom
NDC: 53145-697 | Form: LIQUID
Manufacturer: Menper Distributors, Inc.
Category: otc | Type: HUMAN OTC DRUG LABEL
Date: 20260108

ACTIVE INGREDIENTS: PHENYLEPHRINE HYDROCHLORIDE 10 mg/20 mL; DEXTROMETHORPHAN HYDROBROMIDE 20 mg/20 mL; GUAIFENESIN 400 mg/20 mL
INACTIVE INGREDIENTS: FD&C BLUE NO. 1; GLYCERIN; EDETATE DISODIUM; PROPYL GALLATE; PROPYLENE GLYCOL; SODIUM BENZOATE; ANHYDROUS CITRIC ACID; SORBITOL; FD&C RED NO. 40; SUCRALOSE; XANTHAN GUM; WATER

Mucosan Severe Multi-Symptom

Active ingredients (in each 20 mL) Purpose

Dextromethorphan HBr, 20 mg...........................Cough suppressant

Guaifenesin, 400 mg..........................................Expectorant

Phenylephrine HCl, 10 mg.................................Nasal decongestant

Purposes

Cough suppressant

Expectorant

Nasal descongestant

Uses

- helps loosen phlegm (mucus) and thin bronchial secretions to drain bronchial tubes
- temporarily relieves these symptoms occuring with a cold:
- nasal congestion
- cough due to minor throat and bronquial irritation.

WARNINGS

Do not useif you are now taking a prescription monoamine oxidase inhibitor (MAOI) (certain drugs for depression, psychiatric, or emotional condition, or Parkinson's disease), or for 2 weeks after stopping the MAOI drug. If you do not know if your prescription drug contains an MAOI, ask a doctor or pharmacist before taking this product.

Ask a doctor before use if you have

- heart disease
- high blood pressure
- thyroid disease
- diabetes
- trouble urinating due to an enlarged prostate gland
- cough that occurs with too much phlegm (mucus)
- cough that lasts or is chronic such as occurs with smoking, asthma, chronic bronchitis or emphysema.

Ask a doctor or pharmacist before use if you aretaking any other oral nasal decongestant or stimulant.

OVERDOSAGE

Do not exceed recommended dosage.

Stop use and ask a doctor if

- you get nervous, dizzy or sleepless
- symptoms do not get better within 7 days or are accompanied by fever
- cough lasts more than 7 days, comes back, or is accompanied by fever, rash, or persistant headache. These could be signs of a serious condition.

PREGNANCY OR BREAST FEEDING

If pregnant or breast-feeding,ask a health prefessional before use.

Keep out of reach of children.In case of overdose, get medical help or contact a poison Control Center right away.

Directions

- do not take more than 6 doses in any 24 hour period
- this adult strenght product is not intended for use in children under 12 years of age
- measure only wih doisng cup provided
- keep dosing cup with product
- mL=milliliter

age | dose
adults and children 12 years of age and older | 20 mL every 4 hours
children under 1 years of age | do not use

Other information

- each (20mL) dose contains:sodium 10 mg
- store between 15-30°C (59-86°F)
- do not refrigerate.

Inactive ingredients

anhydrous citric acid, edetate disodium, FD&C blue #1, FD&C red #40, flavors, glycerin, propylene glycol, propyl gallate, purified water, sodium benzoate, sorbitol, sucralose, xanthan gum.

Questions or comments?

1-800-560-5223Monday to Friday 9am-4pm, Eastern Time